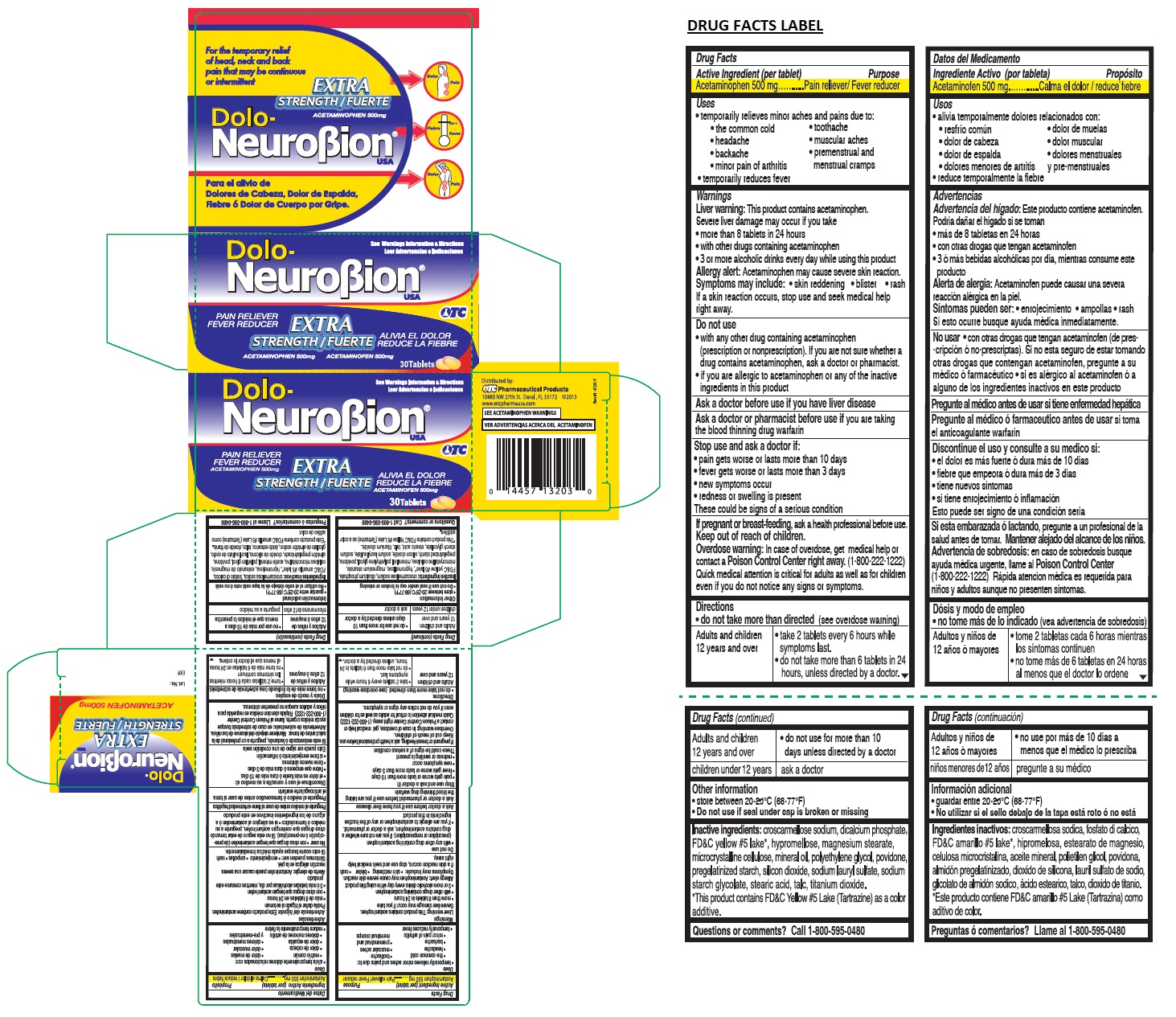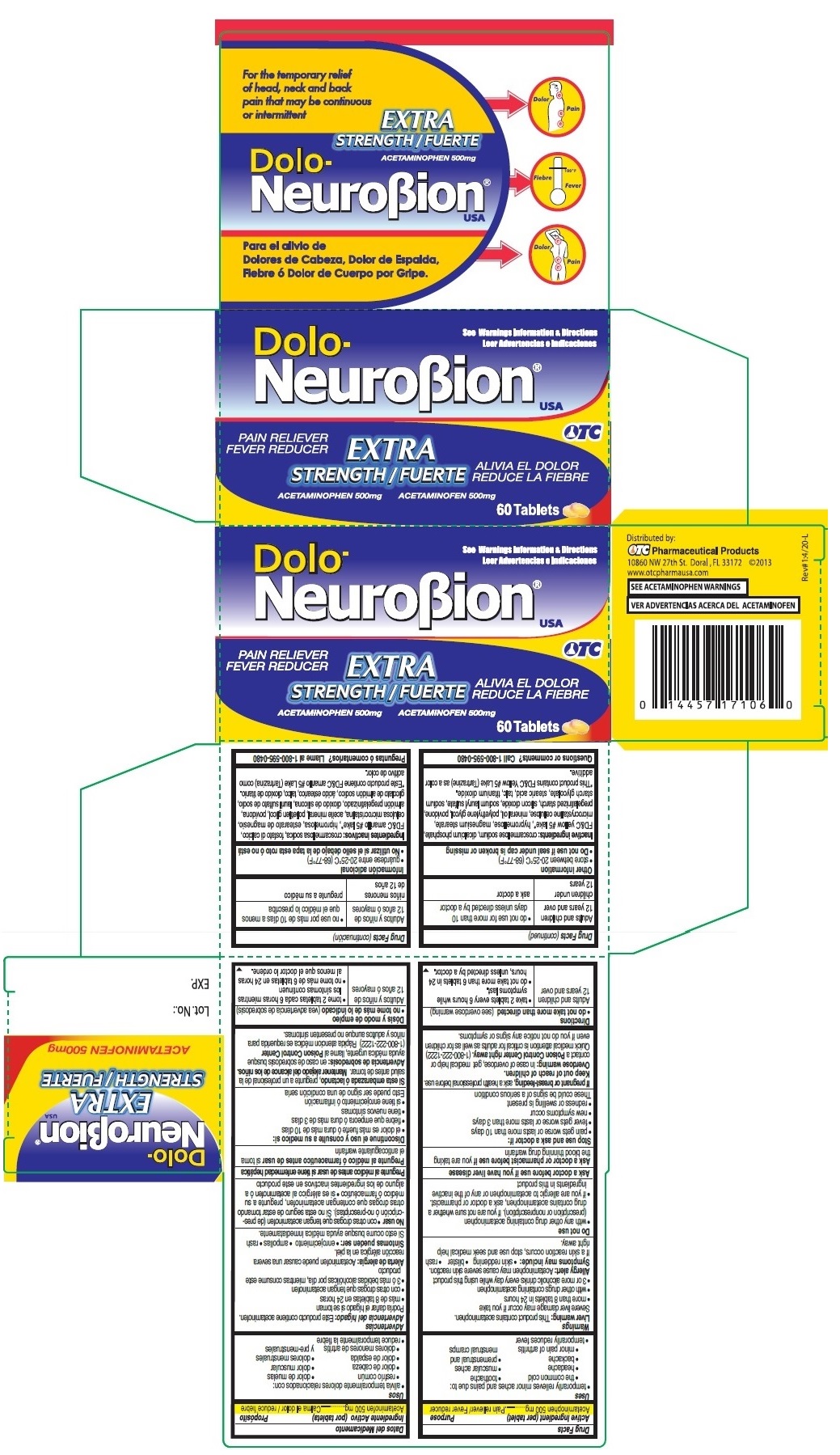 DRUG LABEL: DOLO- NeuroBion
NDC: 55959-171 | Form: TABLET, FILM COATED
Manufacturer: BENARD INDUSTRIES INC
Category: otc | Type: HUMAN OTC DRUG LABEL
Date: 20241104

ACTIVE INGREDIENTS: ACETAMINOPHEN 500 mg/1 1
INACTIVE INGREDIENTS: CROSCARMELLOSE SODIUM; ANHYDROUS DIBASIC CALCIUM PHOSPHATE; FD&C YELLOW NO. 5; HYPROMELLOSE, UNSPECIFIED; MAGNESIUM STEARATE; MICROCRYSTALLINE CELLULOSE; MINERAL OIL; POLYETHYLENE GLYCOL, UNSPECIFIED; POVIDONE, UNSPECIFIED; STARCH, CORN; SILICON DIOXIDE; SODIUM LAURYL SULFATE; SODIUM STARCH GLYCOLATE TYPE A POTATO; STEARIC ACID; TALC; TITANIUM DIOXIDE

Dolo-NeuroBion

Active Ingredient (per tablet)

Acetaminophen 500mg

Purpose

Pain reliever/ Fever reducer

Uses

• temporarily relieves minor aches and pains due to:

• the common cold • toothache

• headache • muscular aches

• backache • premenstrual and menstrual cramps

• minor pain of arthritis

• temporarily reduces fever

Warnings

Liver warning: This product contains acetaminophen.

Severe liver damage may occur if you take

• more than 8 tablets in 24 hours

• with other drugs containing acetaminophen

• 3 or more alcoholic drinks every day while using this product

Allergy alert: Acetaminophen may cause severe skin reaction.

Symptoms may include: • skin reddening • blister • rash

If a skin reaction occurs, stop use and seek medical help right away.

Do not use

• with any other drug containing acetaminophen (prescription or nonprescription). If you are not sure whether a drug contains acetaminophen, ask a doctor or pharmacist

• if you are allergic to acetaminophen or any of the inactive ingredients in this product

Ask a doctor before use if you have liver disease.

Ask a doctor or pharmacist before use if you are taking the blood thinning drug warfarin

Stop use and ask a doctor if:

• pain gets worse or lasts more than 10 days

• fever gets worse or lasts more than 3 days

• new symptoms occur

• redness or swelling is present

These could be signs of a serious condition

If pregnant or breast-feeding, ask a health professional before use.

Keep out of reach of children.

Overdose warning: In case of overdose, get medical help or contact a Poison Control Center right away. (1-800-222-1222)
Quick medical attention is critical for adults as well as for children even if you do not notice any signs or symptoms.

Directions

• do not take more than directed (see overdose warning)

Adults and children 12 years and over | • take 2 tablets every 6 hours while symptoms last.; • do not take more than 6 tablets in 24 hours, unless directed by a doctor.; • do not use for more than 10 days unless directed by a doctor
children under 12 years | ask a doctor

Other information

- store between 20°-25°C (68°-77°F)
- Do not use if seal under cap is broken or missing

Inactive ingredients:

croscarmellose sodium, dicalcium phosphate, FD&C yellow #5 lake*, hypromellose, magnesium stearate, microcrystalline cellulose, mineral oil, polyethylene glycol, povidone, pregelatinized starch, silicon dioxide, sodium lauryl sulfate, sodium starch glycolate, stearic acid, talc, titanium dioxide.

*This product contains FD&C Yellow #5 Lake (Tartrazine) as a color additive.

Questions or comments?

Call 1-800-595-0480

For the temporary relief of head, neck and back pain that may be continuous or intermittent

EXTRA STRENGTH

PAIN RELIEVER
FEVER REDUCER

Distributed by:
OTC Pharmaceutical Products
10860 NW 27th St. Doral, FL 33172 ©2013

www.otcpharmausa.com

SEE ACETAMINOPHEN WARNINGS